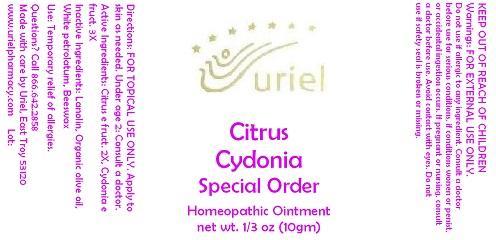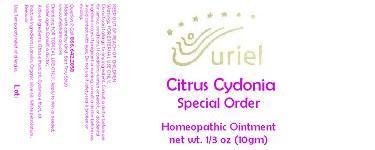 DRUG LABEL: Citrus Cydonia Special Order
NDC: 48951-3176 | Form: OINTMENT
Manufacturer: Uriel Pharmacy Inc.
Category: homeopathic | Type: HUMAN OTC DRUG LABEL
Date: 20141021

ACTIVE INGREDIENTS: LEMON 2 [hp_X]/1 g; QUINCE 3 [hp_X]/1 g
INACTIVE INGREDIENTS: LANOLIN; OLIVE OIL; PETROLATUM; YELLOW WAX

Citrus Cydonia Special Order

INDICATIONS AND USAGE

Directions: FOR TOPICAL USE ONLY.

DOSAGE AND ADMINISTRATION

Apply to skin as needed. Under age 2: Consult a doctor.

ACTIVE INGREDIENT

Active Ingredients: Citrus e fruct. 2X, Cydonia e fruct. 3X

INACTIVE INGREDIENT

Inactive Ingredients: Lanolin, Organic olive oil, White petrolatum, Beeswax

PURPOSE

Use: Temporary relief of allergies.

KEEP OUT OF REACH OF CHILDREN

WARNINGS

Warnings: FOR EXTERNAL USE ONLY. Do not use if allergic to any ingredient. Consult a doctor before use for serious conditions, if conditions worsen or persist, or accidental ingestion occurs. If pregnant or nursing, consult a doctor before use. Avoid contact with eyes. Do not use if safety seal is broken or missing.

QUESTIONS

Questions? Call 866.642.2858 Made with care by Uriel, East Troy 53120 www.urielpharmacy.com